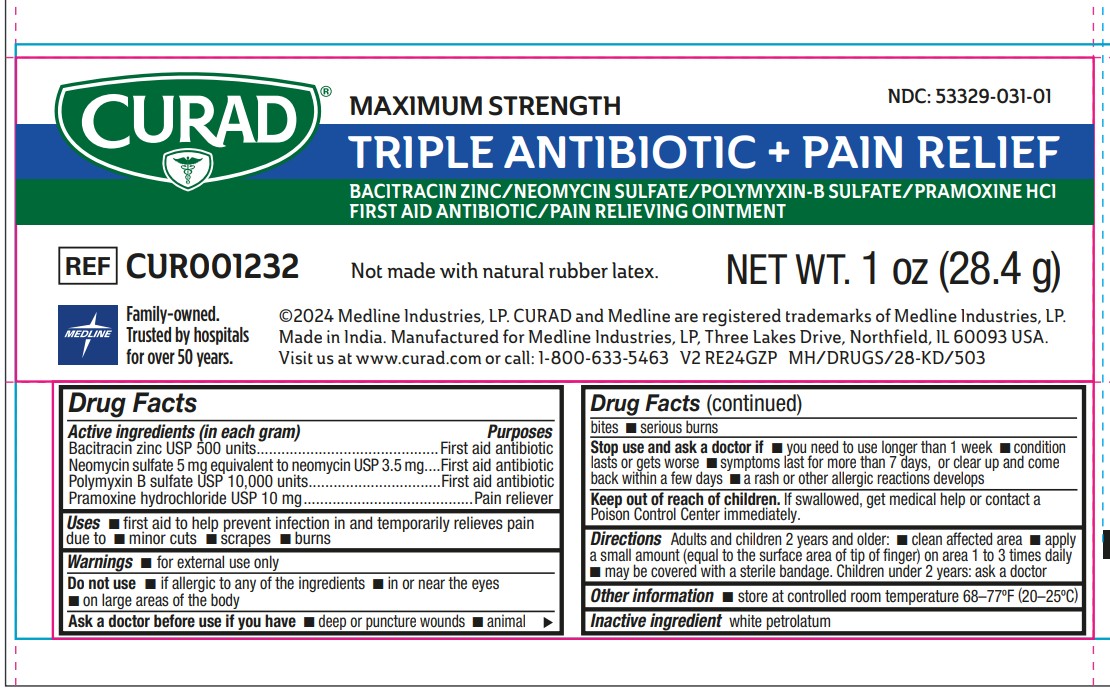 DRUG LABEL: Curad Maximum Strength Triple Antibiotic
NDC: 53329-031 | Form: OINTMENT
Manufacturer: Medline Industries, LP
Category: otc | Type: HUMAN OTC DRUG LABEL
Date: 20250701

ACTIVE INGREDIENTS: POLYMYXIN B SULFATE 10000 [USP'U]/1 g; NEOMYCIN SULFATE 3.5 mg/1 g; PRAMOXINE HYDROCHLORIDE 10 mg/1 g; BACITRACIN ZINC 500 [USP'U]/1 g
INACTIVE INGREDIENTS: WHITE PETROLATUM

031 Curad Maximum Strength Triple Antibiotic

Active ingredients (in each gram)

Bacitracin 500 units

Neomycin 3.5 mg

Polymyxin B 10,000 units

Pramoxin hydrochloride 10 mg

Purposes

First aid antibiotic

First aid antibiotic

First aid antibiotic

Pain reliever

Uses

- First aid to help prevent infection in and temporarily relieves pain due to
- minor cuts
- scrapes
- burns

Warnings

- For external use only

Do not use

- if allergic to any of the ingredients
- in or near the eyes
- on large areas of the body

Ask a doctor before use if you have

- deep or puncture wounds
- animal bites
- serious burns

Stop use and ask a doctor if

- you need to use longer than 1 week
- condition lasts or gets worse
- symptoms last for more than 7 days, or clear up and come back within a few days
- a rash or other allergic reaction develops

Keep out of reach of children.

If swallowed, get medical help or contact a Poison Control Center immediately.

Directions

Adults and children 2 years and older:

- clean affected area
- apply a small amount (equal to the surface area of tip of finger) on area 1 to 3 times daily
- may be covered with a sterile bandage.

Children under 2 years: ask a doctor

Other information

Store at controlled room temperature 68º-77ºF (20º-25ºC).

Inactive ingredient

petrolatum

Manufacturing Information

Manufactured for:

Medline Industries, LP

Three Lakes Drive Northﬁeld, IL 60093 USA

www.curad.com

1-800-MEDLINE (633-5463)

REF: CUR001232